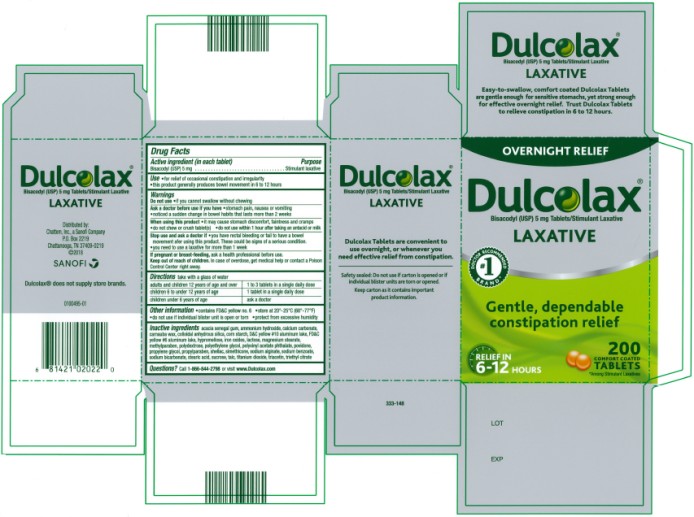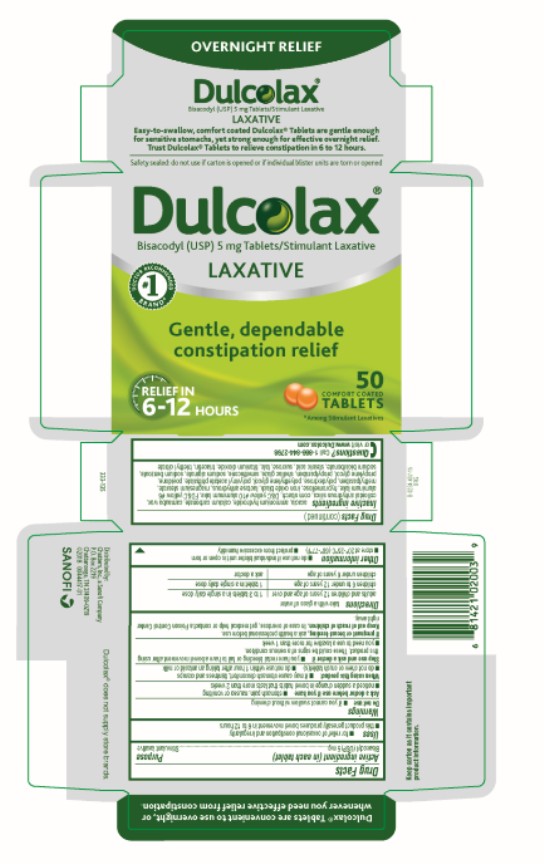 DRUG LABEL: Dulcolax Stimulant Laxative
NDC: 41167-0400 | Form: TABLET, COATED
Manufacturer: Chattem, Inc.
Category: otc | Type: HUMAN OTC DRUG LABEL
Date: 20250408

ACTIVE INGREDIENTS: BISACODYL 5 mg/1 1
INACTIVE INGREDIENTS: ACACIA; CALCIUM CARBONATE; CARNAUBA WAX; STARCH, CORN; FD&C YELLOW NO. 6; D&C YELLOW NO. 10; HYPROMELLOSE, UNSPECIFIED; FERRIC OXIDE RED; LACTOSE, UNSPECIFIED FORM; MAGNESIUM STEARATE; METHYLPARABEN; POLYDEXTROSE; POLYETHYLENE GLYCOL, UNSPECIFIED; Polyvinyl Acetate Phthalate; POVIDONE; PROPYLENE GLYCOL; PROPYLPARABEN; SHELLAC; SODIUM ALGINATE; SODIUM BENZOATE; SODIUM BICARBONATE; STEARIC ACID; SUCROSE; TALC; TITANIUM DIOXIDE; TRIACETIN; TRIETHYL CITRATE

Dulcolax Stimulant Laxative

Dulcolax Stimulant Laxative Tablets

Drug Facts

Active ingredient (in each tablet)

Bisacodyl (USP) 5 mg

Purpose

Stimulant laxative

Use

● for relief of occasional constipation and irregularity

● this product generally produces bowel movement in 6 to 12 hours

Warnings

Do not use

● if you cannot swallow without chewing

Ask a doctor before use if you have

● stomach pain, nausea or vomiting

● noticed a sudden change in bowel habits that lasts more than 2 weeks

When using this product

● it may cause stomach discomfort, faintness and cramps

● do not chew or crush tablet(s)

● do not use within 1 hour after taking an antacid or milk

Stop use and ask a doctor if

● you have rectal bleeding or fail to have a bowel movement after using this product. These could be signs of a serious condition.

● you need to use a laxative for more than 1 week

If pregnant or breast-feeding,

ask a health professional before use.

Keep out of reach of children.

In case of overdose, get medical help or contact a Poison Control Center right away.

Directions

take with a glass of water
adults and children 12 years of age and over | 1 to 3 tablets in a single daily dose
children 6 to under 12 years of age | 1 tablet in a single daily dose
children under 6 years of age | ask a doctor

Other information

● contains FD&C Yellow No. 6

● do not use if individual blister unit is open or torn

● store at 20°-25°C (68°-77°F)

● protect from excessive humidity

Inactive ingredients

acacia senegal gum, ammonium hydroxide, calcium carbonate, carnauba wax, colloidal anhydrous silica, corn starch, D&C yellow #10 aluminum lake, FD&C yellow #6 aluminum lake, hypromellose, iron oxides, lactose, magnesium stearate, methylparaben, polydextrose, polyethylene glycol, polyvinyl acetate phthalate, povidone, propylene glycol, propylparaben, shellac, simethicone, sodium alginate, sodium benzoate, sodium bicarbonate, stearic acid, sucrose, talc, titanium dioxide, triacetin, triethyl citrate

Questions?

Call 1-866-844-2798 or visit www.Dulcolax.com

Keep carton as it contains important product information.

Dulcolax Stimulant Laxative Tablets

Drug Facts

Active ingredient (in each tablet)

Bisacodyl (USP) 5 mg

Purpose

Stimulant laxative

Use

● for relief of occasional constipation and irregularity

● this product generally produces bowel movement in 6 to 12 hours

Warnings

Do not use

● if you cannot swallow without chewing

Ask a doctor before use if you have

● stomach pain, nausea or vomiting

● noticed a sudden change in bowel habits that lasts more than 2 weeks

When using this product

● it may cause stomach discomfort, faintness and cramps

● do not chew or crush tablet(s) ● do not use within 1 hour after taking an antacid or milk

Stop use and ask a doctor if

● you have rectal bleeding or fail to have a bowel movement after using this product. These could be signs of a serious condition.

● you need to use a laxative for more than 1 week

If pregnant or breast-feeding,

ask a health professional before use.

Keep out of reach of children.

In case of overdose, get medical help or contact a Poison Control Center right away.

Directions

take with a glass of water
adults and children 12 years of age and over | 1 to 3 tablets in a single daily dose
children 6 to under 12 years of age | 1 tablet in a single daily dose
children under 6 years of age | ask a doctor

Other information

● contains FD&C Yellow No. 6

● do not use if individual blister unit is open or torn

● store at 20°-25°C (68°-77°F)

● protect from excessive humidity

Inactive ingredients

acacia senegal gum, ammonium hydroxide, calcium carbonate, carnauba wax, colloidal anhydrous silica, corn starch, D&C yellow #10 aluminum lake, FD&C yellow #6 aluminum lake, hypromellose, iron oxides, lactose, magnesium stearate, methylparaben, polydextrose, polyethylene glycol, polyvinyl acetate phthalate, povidone, propylene glycol, propylparaben, shellac, simethicone, sodium alginate, sodium benzoate, sodium bicarbonate, stearic acid, sucrose, talc, titanium dioxide, triacetin, triethyl citrate

Questions?

Call 1-866-844-2798 or visit www.Dulcolax.com

Keep carton as it contains important product information.

PRINCIPAL DISPLAY PANEL

Dulcolax
LAXATIVE
200 TABLETS

PRINCIPAL DISPLAY PANEL

Dulcolax
LAXATIVE
50 TABLETS